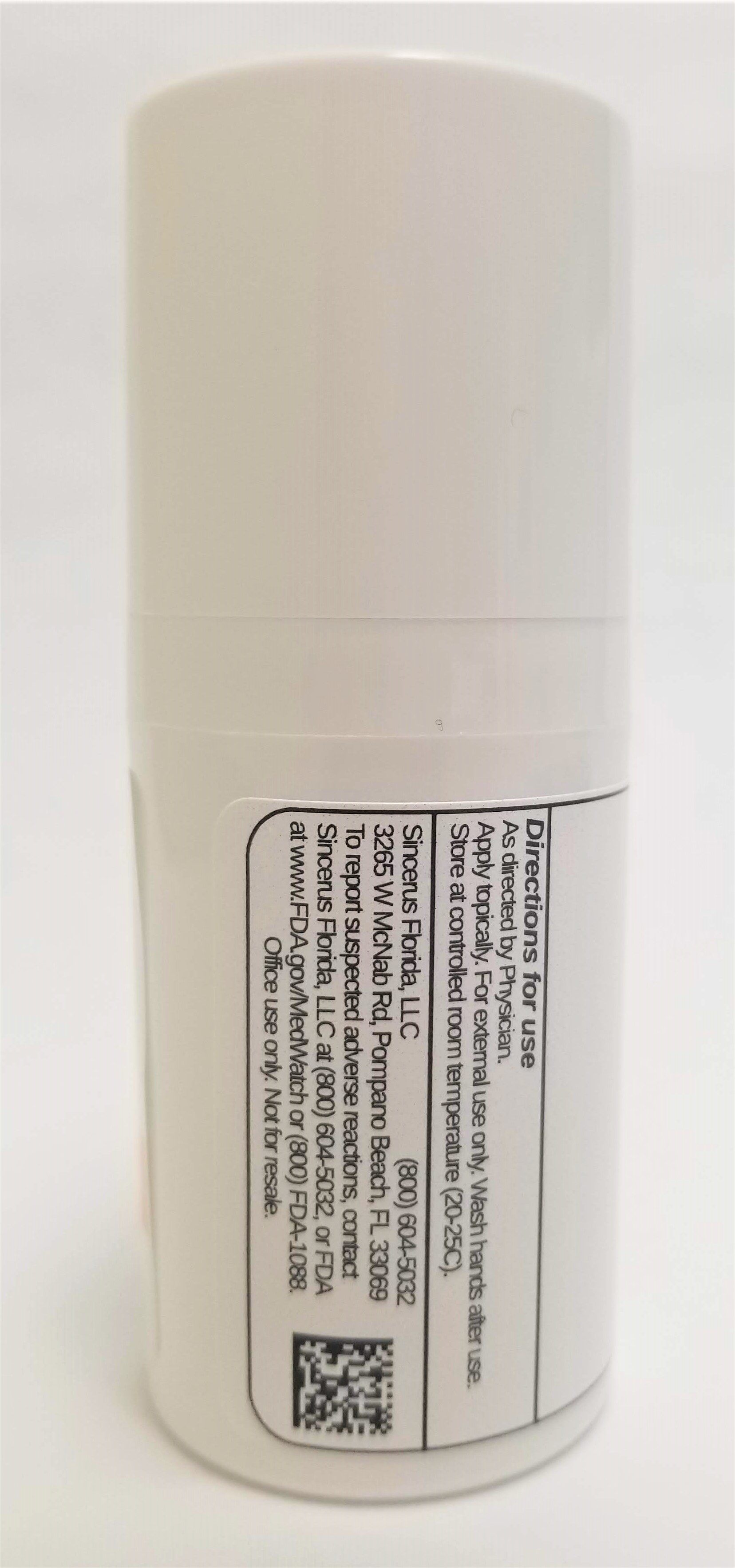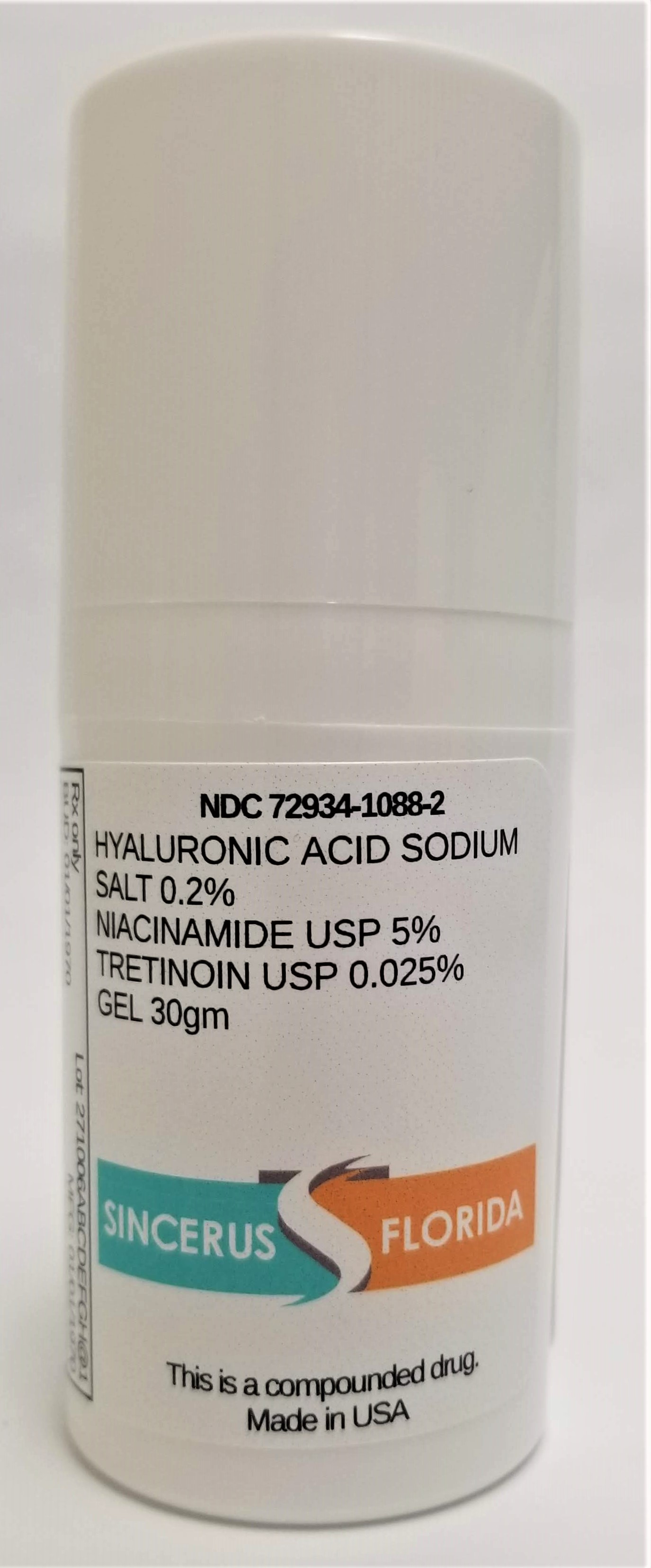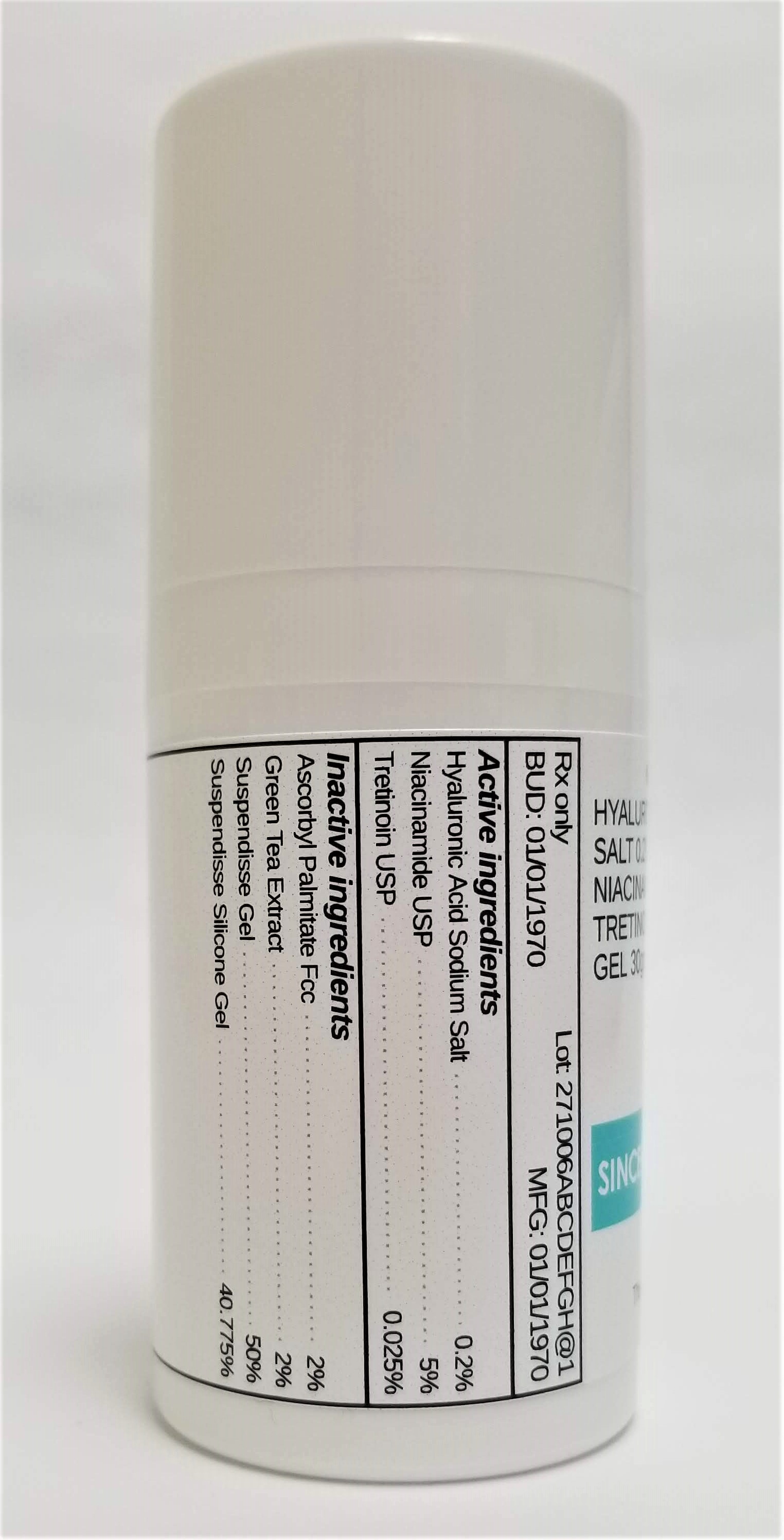 DRUG LABEL: ASCORBYL PALMITATE 2% / HYALURONIC ACID SODIUM SALT 0.2% / NIACINAMIDE 5% / TRETINOIN 0.025%
NDC: 72934-1088 | Form: GEL
Manufacturer: Sincerus Florida, LLC
Category: prescription | Type: HUMAN PRESCRIPTION DRUG LABEL
Date: 20190517

ACTIVE INGREDIENTS: NIACINAMIDE 5 g/100 g; TRETINOIN 0.025 g/100 g; HYALURONATE SODIUM 0.2 g/100 g

HYALURONIC ACID SODIUM SALT 0.2% / NIACINAMIDE 5% / TRETINOIN 0.025%